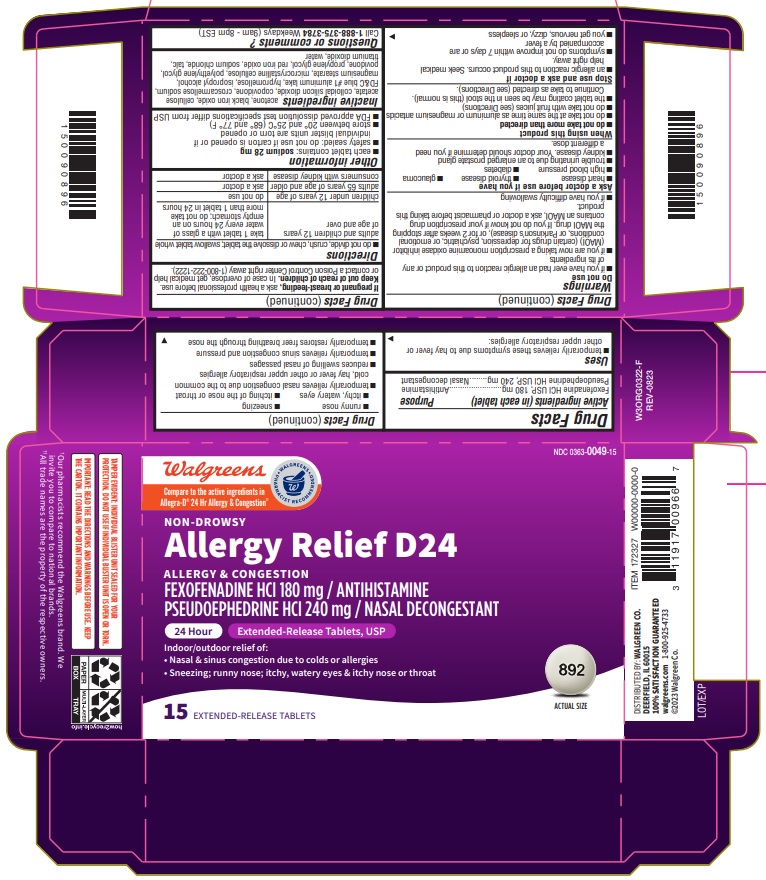 DRUG LABEL: Fexofenadine HCl and Pseudoephedrine HCl
NDC: 0363-0049 | Form: TABLET, EXTENDED RELEASE
Manufacturer: Walgreens company
Category: otc | Type: HUMAN OTC DRUG LABEL
Date: 20250722

ACTIVE INGREDIENTS: FEXOFENADINE HYDROCHLORIDE 180 mg/1 1; PSEUDOEPHEDRINE HYDROCHLORIDE 240 mg/1 1
INACTIVE INGREDIENTS: ACETONE; CROSCARMELLOSE SODIUM; CELLULOSE ACETATE; COPOVIDONE; HYPROMELLOSES; CELLULOSE, MICROCRYSTALLINE; Polyethylene Glycol, Unspecified; TALC; TITANIUM DIOXIDE; SILICON DIOXIDE; ISOPROPYL ALCOHOL; FD&C BLUE NO. 1 ALUMINUM LAKE; MAGNESIUM STEARATE; WATER; SODIUM CHLORIDE; FERRIC OXIDE RED; POVIDONE K30; PROPYLENE GLYCOL; FERROSOFERRIC OXIDE

Fexofenadine HCl 180 mg and Pseudoephedrine HCI 240 mg ER Tablets, USP

Active ingredient(s)

Fexofenadine HCl USP, 180 mg

Pseudoephedrine HCl USP, 240 mg

Purpose

Antihistamine

Nasal decongestant

Use(s)

- temporarily relieves these symptoms due to hay fever or other upper respiratory allergies:
- runny nose
- sneezing
- itchy, watery eyes
- itching of the nose or throat
- temporarily relieves nasal congestion due to the common cold, hay fever or other upper respiratory allergies
- reduces swelling of nasal passages
- temporarily relieves sinus congestion and pressure
- temporarily restores freer breathing through the nose

Warnings

Do not use

- if you have ever had an allergic reaction to this product or any of its ingredients
- if you are now taking a prescription monoamine oxidase inhibitor (MAOI) (certain drugs for depression, psychiatric, or emotional conditions, or Parkinson’s disease), or for 2 weeks after stopping the MAOI drug. If you do not know if your prescription drug contains an MAOI, ask a doctor or pharmacist before taking this product.
- if you have difficulty swallowing

Ask a doctor before use if you have

- heart disease
- thyroid disease
- glaucoma
- high blood pressure
- diabetes
- trouble urinating due to an enlarged prostate gland
- kidney disease. Your doctor should determine if you need a different dose.

When using this product

- do not take more than directed
- do not take at the same time as aluminum or magnesium antacids
- do not take with fruit juices (see Directions)
- the tablet coating may be seen in the stool (this is normal). Continue to take as directed (see Directions).

Stop use and ask doctor if

- an allergic reaction to this product occurs. Seek medical help right away.
- symptoms do not improve within 7 days or are accompanied by a fever
- you get nervous, dizzy, or sleepless

If pregnant or breast-feeding,

ask a health professional before use.

Keep out of reach of children

In case of overdose, get medical help or contact a Poison Control Center right away.

Directions

- do not divide, crush, chew or dissolve the tablet; swallow tablet whole

adults and children 12 years of age and over | take 1 tablet with a glass of water every 24 hours on an empty stomach; do not take more than 1 tablet in 24 hours
children under 12 years of age | do not use
adults 65 years of age and older | ask a doctor
consumers with kidney disease | ask a doctor

Other information

- each tablet contains: 28 mg sodium
- safety sealed: do not use if carton is opened or if individual blister units are torn or opened
- store between 20° - 25°C (68° - 77°F)
- FDA approved dissolution test specifications differ from USP

Inactive ingredients

acetone, black iron oxide, cellulose acetate, colloidal silicon dioxide, copovidone, croscarmellose sodium, FD&C blue #1 aluminum lake, hypromellose, isopropyl alcohol, magnesium stearate, microcrystalline cellulose, polyethylene glycol, povidone, propylene glycol, red iron oxide, sodium chloride, talc, titanium dioxide, water

Questions?

Questions? Call 1-888-375-3784 Weekdays (9am - 8pm EST)

Distributed by:

Dr. Reddy’s Laboratories, Inc.

Princeton, NJ 08540